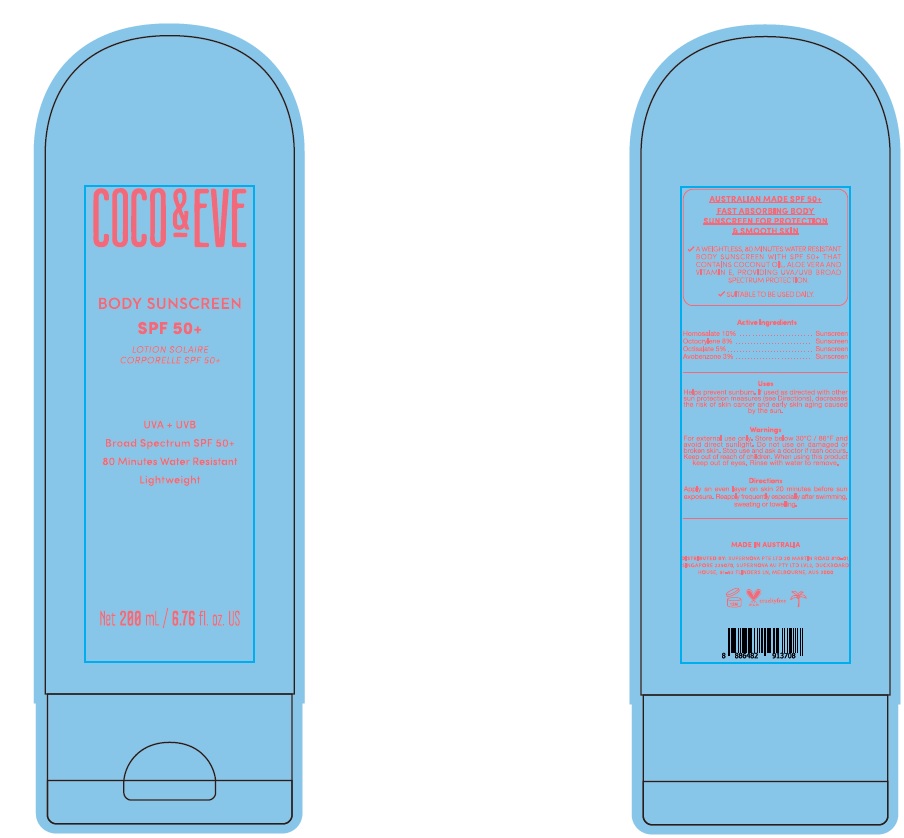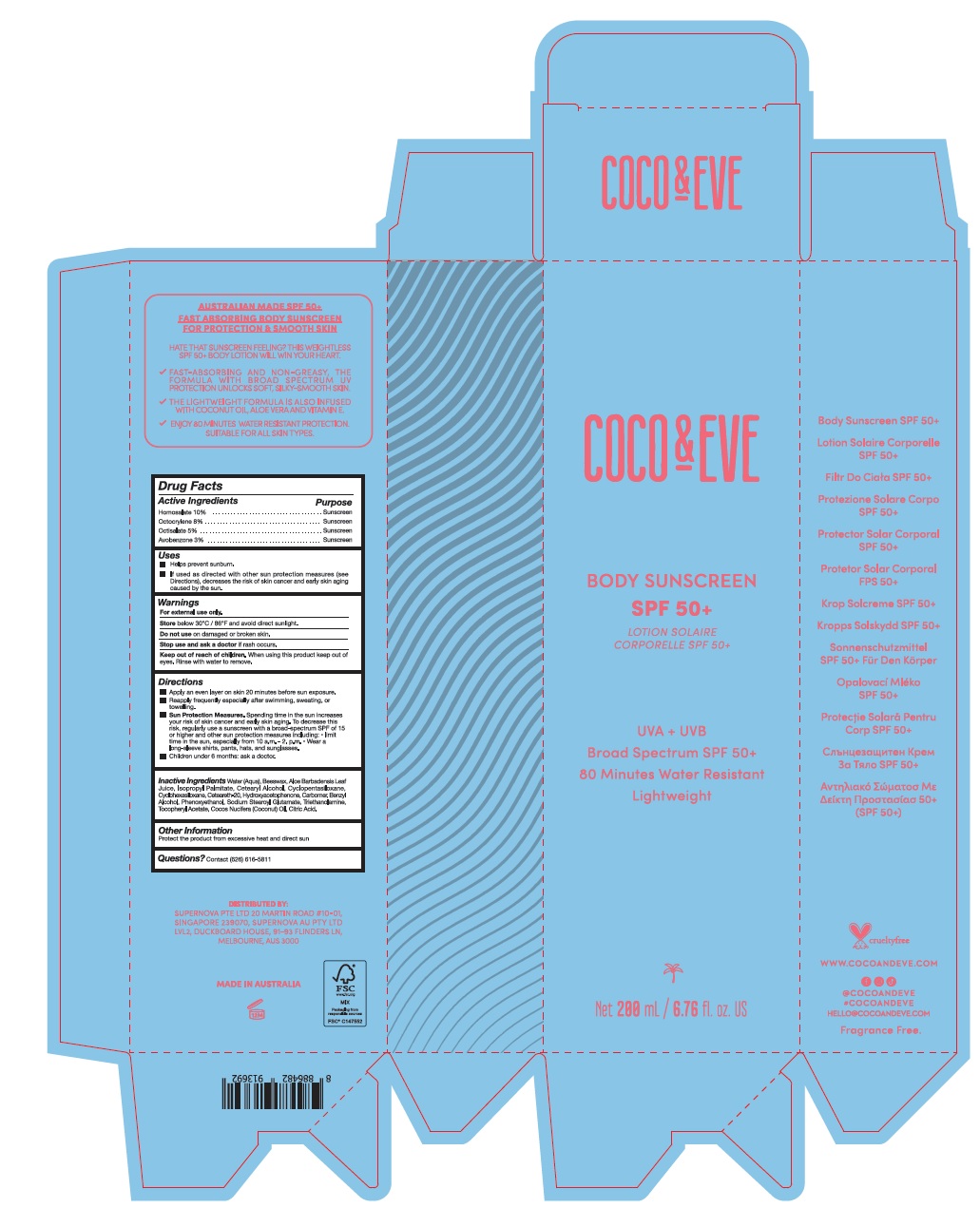 DRUG LABEL: COCO  EVE BODY SUNSCREEN SPF50 plus
NDC: 82931-003 | Form: LOTION
Manufacturer: Supernova USA Inc.
Category: otc | Type: HUMAN OTC DRUG LABEL
Date: 20221116

ACTIVE INGREDIENTS: HOMOSALATE 10 g/100 mL; OCTOCRYLENE 8 g/100 mL; OCTISALATE 5 g/100 mL; AVOBENZONE 3 g/100 mL
INACTIVE INGREDIENTS: WATER; YELLOW WAX; ALOE VERA LEAF; ISOPROPYL PALMITATE; CETOSTEARYL ALCOHOL; CYCLOMETHICONE 5; CYCLOMETHICONE 6; POLYOXYL 20 CETOSTEARYL ETHER; HYDROXYACETOPHENONE; CARBOMER HOMOPOLYMER, UNSPECIFIED TYPE; BENZYL ALCOHOL; PHENOXYETHANOL; SODIUM STEAROYL GLUTAMATE; TROLAMINE; .ALPHA.-TOCOPHEROL ACETATE; COCONUT OIL; CITRIC ACID MONOHYDRATE

COCO & EVE BODY SUNSCREEN SPF 50+

Drug Facts

Active Ingredients
Homosalate 10%
Octocrylene 8%
Octisalate 5%
Avobenzone 3%

Purpose
Sunscreen
Sunscreen
Sunscreen
Sunscreen

Uses

- Helps prevent sunburn.
- If used as directed with other sun protection measures (see Directions), decreases the risk of skin cancer and early skin aging caused by the sun.

Warnings

For external use only.

Store below 30°C / 86°F and avoid direct sunlight.

Do not use on damaged or broken skin.

Stop use and ask a doctor if rash occurs.

Keep out of reach of children. When using this product keep out of eyes. Rinse with water to remove.

Directions

- Apply an even layer on skin 20 minutes before sun exposure.
- Reapply frequently especially after swimming, swaeting, or towelling.
- Sun Protection Measures. Spending time in the sun increases your risk of skin cancer and early skin aging. To decrease this risk, regularly use a sunscreen with a broad-spectrum SPF of 15 or higher and other sun protection measures including:
  - limit time in the sun, especially from 10 a.m. - 2. p.m.
  - Wear a long-sleeve shirts, pants, hats, and sunglasses.
- Children under 6 months: ask a doctor.

Inactive ingredients

Water (Aqua), Beeswax, Aloe Barbadensis Leaf Juice, Isopropyl Palmitate, Cetearyl Alcohol, Cyclopentasiloxane, Cyclohexasiloxane, Ceteareth-20, Hydroxyacetophenone, Carbomer, Benzyl Alocohol, Phenoxyethanol, Sodium Stearoyl Glutamate, Triethanolamine, Tocopheryl Acetate, Cocos Nucifera (Coconut) Oil, Citric Acid.

Other information

Protect the product from excessive heat and direct sun

Questions? Contact (626) 616-5811

PRINCIPAL DISPLAY PANEL

COCO & EVE

BODY SUNSCREEN

SPF 50+

LOTION SOLAIRE
CORPORELLE SPF 50+

UVA + UVB

Broad Spectrum SPF 50+

80 Minutes Water Resistant

Lightweight

Net 200 mL / 6.76 fl. oz. US

COCO & EVE

BODY SUNSCREEN

SPF 50+

LOTION SOLAIRE
CORPORELLE SPF 50+

UVA + UVB

Broad Spectrum SPF 50+

80 Minutes Water Resistant

Lightweight

Net 200 mL / 6.76 fl. oz. US